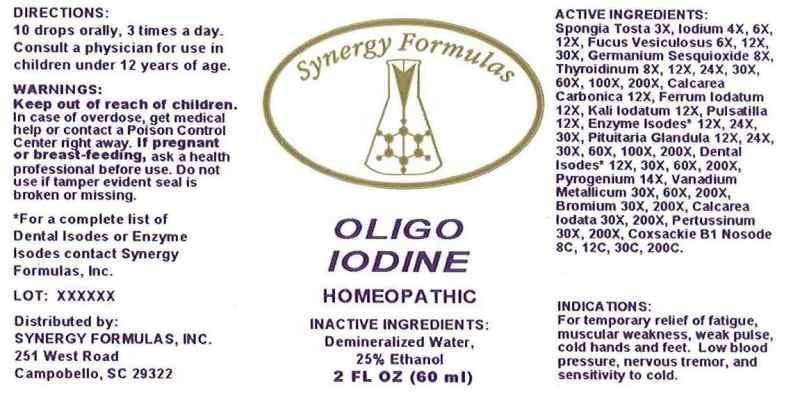 DRUG LABEL: Oligo Iodine
NDC: 43772-0041 | Form: LIQUID
Manufacturer: Synergy Formulas, Inc.
Category: homeopathic | Type: HUMAN OTC DRUG LABEL
Date: 20140716

ACTIVE INGREDIENTS: SPONGIA OFFICINALIS SKELETON, ROASTED 3 [hp_X]/1 mL; IODINE 4 [hp_X]/1 mL; FUCUS VESICULOSUS 6 [hp_X]/1 mL; GERMANIUM SESQUIOXIDE 8 [hp_X]/1 mL; SUS SCROFA THYROID 8 [hp_X]/1 mL; OYSTER SHELL CALCIUM CARBONATE, CRUDE 12 [hp_X]/1 mL; FERROUS IODIDE 12 [hp_X]/1 mL; POTASSIUM IODIDE 12 [hp_X]/1 mL; PULSATILLA VULGARIS 12 [hp_X]/1 mL; BOS TAURUS PITUITARY GLAND 12 [hp_X]/1 mL; CYSTEINE 12 [hp_X]/1 mL; SODIUM DIETHYL OXALACETATE 12 [hp_X]/1 mL; FUMARIC ACID 12 [hp_X]/1 mL; .ALPHA.-KETOGLUTARIC ACID 12 [hp_X]/1 mL; MANGANESE GLUCONATE 12 [hp_X]/1 mL; SILVER 12 [hp_X]/1 mL; GOLD 12 [hp_X]/1 mL; COPPER 12 [hp_X]/1 mL; CLOVE 12 [hp_X]/1 mL; FORMALDEHYDE 12 [hp_X]/1 mL; LIDOCAINE 12 [hp_X]/1 mL; MERCURIUS SOLUBILIS 12 [hp_X]/1 mL; MOLYBDENUM 12 [hp_X]/1 mL; NICKEL 12 [hp_X]/1 mL; PALLADIUM 12 [hp_X]/1 mL; TIN 12 [hp_X]/1 mL; TITANIUM 12 [hp_X]/1 mL; ZINC 12 [hp_X]/1 mL; RANCID BEEF 14 [hp_X]/1 mL; VANADIUM 30 [hp_X]/1 mL; BROMINE 30 [hp_X]/1 mL; CALCIUM IODIDE 30 [hp_X]/1 mL; HUMAN SPUTUM, BORDETELLA PERTUSSIS INFECTED 30 [hp_X]/1 mL; HUMAN COXSACKIEVIRUS B1 8 [hp_X]/1 mL
INACTIVE INGREDIENTS: WATER; ALCOHOL

DRUG FACTS

ACTIVE INGREDIENTS:

Spongia Tosta 3X, 4X, 6X, 12X, Fucus Vesiculosus 6X, 12X, 30X, Germanium Sequioxide 8X, Thyroidinum (suis) 8X, 12X, 24X, 30X, 60X,100X, 200X, Calcarea Carbonica 12X, Ferrum Iodatum 12X, Kali Iodatum 12X, Pulsatilla (vulgaris) 12X, Pituitaria Glandula(Bovine) 12X, 24X, 30X, 60X, 100X, 200X, Cysteinum 12X, 24X, 30X, Natrum Oxalaceticum 12X, 24X, 30X, Fumaricum Acidum 12X, 24X, 30X, Alpha-Ketoglutaricum Acidum 12X, 24X, 30X, Manganese Gluconate 12X, 24X, 30C, Argentum Metallicum 12X, 30X, 60X, 200X, Aurum Metallicum 12X, 30X, 60X, 200X, Cuprum Metallicum 12X, 30X, 60X, 200X, Eugenia Caryophyllata Eugenol 12X, 30X, 60X, 200X, Formalinum 12X, 30X, 60X, 200X, Lidocaine 12X, 30X, 60X, 200X, Mercurius Solubilis 12X, 30X, 60X, 200X, Molybdenum Metallicum 12X, 30X, 60X, 200X, Niccolum Metallicum 12X, 30X,60X, 200X, Palladium Metallicum 12X, 30X, 60X, 200X, Stannum Metallicum 12X, 30X, 60X, 200X, Titanium Metallicum 12X, 30X, 60X, 200X, Zincum Metallicum 12X, 30X, 60X, 200X, Pyrogenium 14X, Vanadium Metallicum 30X, 60X, 200X, Bromium 30X, 200X, Calcarea Iodata 30X, 200X, Pertussinum 30X, 200X, Coxsackie B1 Nosode 8C, 12C, 30C, 200C,

INDICATIONS:

For temporary relief of fatigue, muscular weakness, weak pulse, cold hands and feet. Low blood pressure, nervous tremor, and sensitivity to cold.

WARNINGS:

Keep out of reach of children. In case of overdose, get medical help or contact a Poison Control Center right away.

If pregnant or breast-feeding, ask a health professional before use.

Do not use if tamper evident seal is broken or missing.

KEEP OUT OF REACH OF CHILDREN. In case of overdose, get medical help or contact a Poison Control Center right away.

DIRECTIONS:

10 drops orally, 3 times a day. Consult a physician for use in children under 12 years of age.

INDICATIONS:

For temporary relief of fatigue, muscular weakness, weak pulse, cold hands and feet. Low blood pressure, nervous tremor, and sensitivity to cold.

INACTIVE INGREDIENTS:

Demineralized Water, 25% Ethanol

QUESTIONS:

Distributed by:

SYNERGY FORMULAS, INC

251 West Road

Campobello, SC 29322

*For complete list of Dental Isodes or Enzyme Isodes contact Synergy

Formulas, Inc.

PACKAGE LABEL DISPLAY:

Synergy Formulas

OLIGO IODINE

HOMEOPATHIC

2 FL OZ (60 ml)